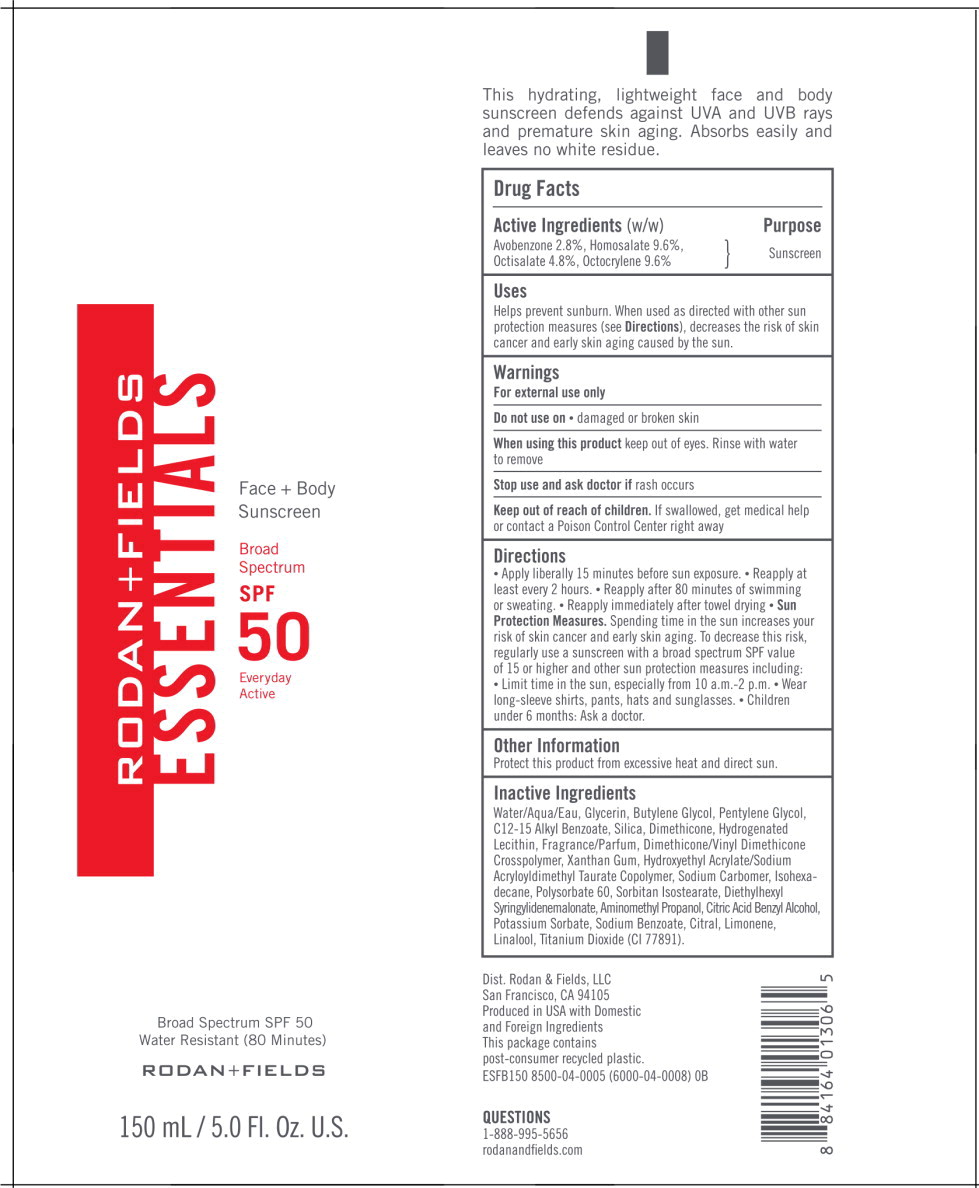 DRUG LABEL: ESSENTIALS Face and Body Sunscreen
NDC: 14222-0002 | Form: LOTION
Manufacturer: Rodan & Fields
Category: otc | Type: HUMAN OTC DRUG LABEL
Date: 20200402

ACTIVE INGREDIENTS: AVOBENZONE 0.028 g/1 mL; HOMOSALATE 0.096 g/1 mL; OCTISALATE 0.048 g/1 mL; OCTOCRYLENE 0.096 g/1 mL
INACTIVE INGREDIENTS: AMINOMETHYLPROPANOL; BENZYL ALCOHOL; BUTYLENE GLYCOL; ALKYL (C12-15) BENZOATE; CITRIC ACID MONOHYDRATE; DIETHYLHEXYL SYRINGYLIDENEMALONATE; DIMETHICONE; DIMETHICONE/VINYL DIMETHICONE CROSSPOLYMER (SOFT PARTICLE); GLYCERIN; HYDROGENATED SOYBEAN LECITHIN; HYDROXYETHYL ACRYLATE/SODIUM ACRYLOYLDIMETHYL TAURATE COPOLYMER (100000 MPA.S AT 1.5%); ISOHEXADECANE; PENTYLENE GLYCOL; POLYSORBATE 60; POTASSIUM SORBATE; SILICON DIOXIDE; SODIUM BENZOATE; CARBOXYPOLYMETHYLENE; SORBITAN ISOSTEARATE; TITANIUM DIOXIDE; WATER; XANTHAN GUM; LINALOOL, (+/-)-; CITRAL

Drug Facts

Active Ingredients (w/w)

Avobenzone 2.8%, Homosalate 9.6%, Octisalate 4.8%, Octocrylene 9.6%

Purpose

Sunscreen

Uses

Helps prevent sunburn. When used as directed with other sun protection measures (see Directions), decreases the risk of skin cancer and early skin aging caused by the sun.

Warnings

For external use only

Do not use on

- damaged or broken skin

When using this product keep out of eyes. Rinse with water to remove

Stop use and ask doctor if rash occurs

Keep out of reach of children. If swallowed, get medical help or contact a Poison Control Center right away

Directions

- Apply liberally 15 minutes before sun exposure.
- Reapply at least every 2 hours.
- Reapply after 80 minutes of swimming or sweating.
- Reapply immediately after towel drying
- Sun Protection Measures. Spending time in the sun increases your risk of skin cancer and early skin aging. To decrease this risk, regularly use a sunscreen with a broad spectrum SPF value of 15 or higher and other sun protection measures including:
  - Limit time in the sun, especially from 10 a.m.-2 p.m.
  - Wear long-sleeve shirts, pants, hats and sunglasses.
- Children under 6 months: Ask a doctor.

Other Information

Protect this product from excessive heat and direct sun.

Inactive Ingredients

Water/Aqua/Eau, Glycerin, Butylene Glycol, Pentylene Glycol, C12-15 Alkyl Benzoate, Silica, Dimethicone, Hydrogenated Lecithin, Fragrance/Parfum, Dimethicone/Vinyl Dimethicone Crosspolymer, Xanthan Gum, Hydroxyethyl Acrylate/Sodium Acryloyldimethyl Taurate Copolymer, Sodium Carbomer, Isohexadecane, Polysorbate 60, Sorbitan Isostearate, Diethylhexyl Syringylidenemalonate, Aminomethyl Propanol, Citric Acid Benzyl Alcohol, Potassium Sorbate, Sodium Benzoate, Citral, Limonene, Linalool, Titanium Dioxide (CI 77891).

Principal Display Panel – 150 mL Carton Label

RODAN+FIELDS

ESSENTIALS

Face + Body
Sunscreen

Broad
Spectrum

SPF
50

Everyday
Active

Broad Spectrum SPF 50
Water Resistant (80 Minutes)

RODAN + FIELDS

150 mL/5.0 Fl. Oz. U.S.